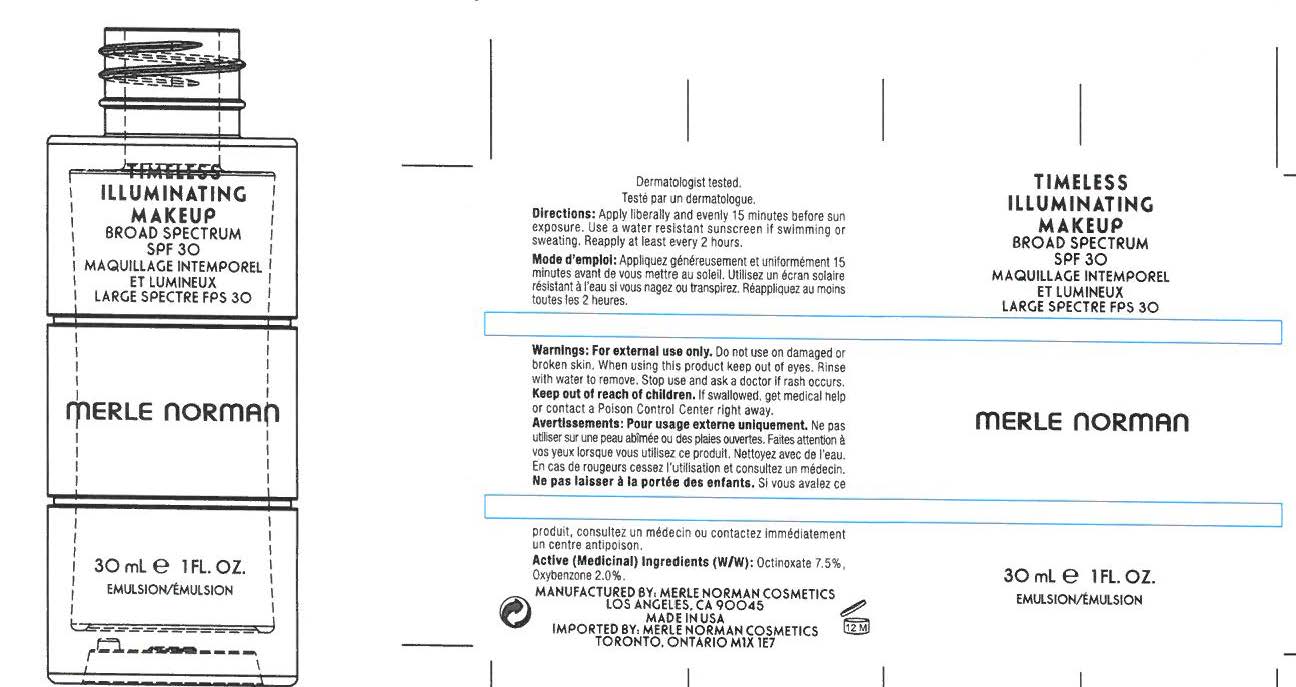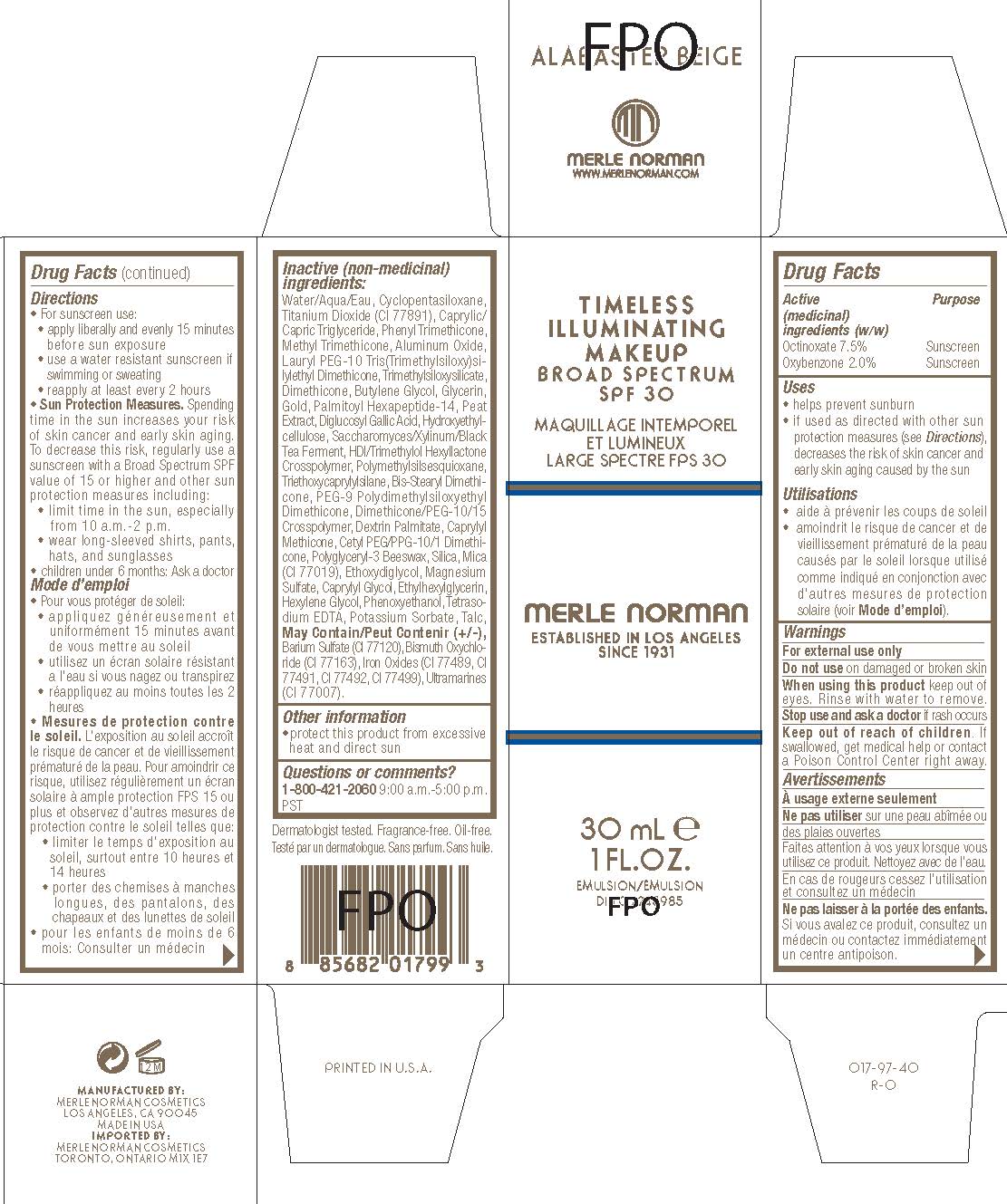 DRUG LABEL: Timeless Illuminating Makeup SPF 30  Porcelain
NDC: 57627-173 | Form: CREAM
Manufacturer: Merle Norman Cosmetics, Inc
Category: otc | Type: HUMAN OTC DRUG LABEL
Date: 20251119

ACTIVE INGREDIENTS: OCTINOXATE 7.5 g/100 mL; OXYBENZONE 2 g/100 mL
INACTIVE INGREDIENTS: WATER; CYCLOMETHICONE 5; TITANIUM DIOXIDE; MEDIUM-CHAIN TRIGLYCERIDES; PHENYL TRIMETHICONE; METHYL TRIMETHICONE; ALUMINUM OXIDE; TRIMETHYLSILOXYSILICATE (M/Q 0.6-0.8); DIMETHICONE; BUTYLENE GLYCOL; GLYCERIN; GOLD; HYDROXYETHYL CELLULOSE (100 MPA.S AT 2%); HEXAMETHYLENE DIISOCYANATE/TRIMETHYLOL HEXYLLACTONE CROSSPOLYMER; POLYMETHYLSILSESQUIOXANE (4.5 MICRONS); TRIETHOXYCAPRYLYLSILANE; PEG-9 POLYDIMETHYLSILOXYETHYL DIMETHICONE; DEXTRIN PALMITATE (CORN; 20000 MW); CAPRYLYL TRISILOXANE; CETYL PEG/PPG-10/1 DIMETHICONE (HLB 2); SILICON DIOXIDE; MICA; DIETHYLENE GLYCOL MONOETHYL ETHER; MAGNESIUM SULFATE, UNSPECIFIED FORM; CAPRYLYL GLYCOL; ETHYLHEXYLGLYCERIN; HEXYLENE GLYCOL; PHENOXYETHANOL; EDETATE SODIUM; POTASSIUM SORBATE; TALC; BARIUM SULFATE; BISMUTH OXYCHLORIDE; FERROUS OXIDE; FERRIC OXIDE RED; FERRIC OXIDE YELLOW; FERROSOFERRIC OXIDE; ULTRAMARINE BLUE

Timeless Illuminating Makeup Broad Spectrum SPF 30 Porcelain

ASK DOCTOR

Active Ingredients Purpose

Octinoxate 7.5% Sunscreen

Oxybenzone 2.0% Sunscreen

Uses

- helps prevent sunburn
- if used as directed with other sun protection measures (see Directions), decreases the risk of skin cancer and early skin aging caused by the sun

Keep out of reach of children.If swallowed, get medical help or contact a Poison Control Center right away.

Stop use and ask a doctorif rash occurs

Warnings

For external use only

- Do not useon domaged or broken skin
- When using this productkeep out of eyes. Rinse with water to remove.

Directions

- For sunscreen use:

- apply liberally and evenly 15 minutes before sun exposure

- use a water resistant sunscreen if swimming or sweating

- Reapply at least every 2 hours

- Sun Protection Measures.Spending time in the sun increases your risk of skin cancer and early skin aging. To decrease this risk, regulary use a sunscreeen with a Broad Spectrum SPF value of 15 or higher and other sun protection measures including:

- limit tim in the sun, especially from 10a.m. - 2p.m.

- wear long-sleeved shirts, pants, hats, and sunglasses

- children under 6 months: Ask a doctor

INACTIVE INGREDIENT

Water/Aqua/Eau, Cyclopentasiloxane, Tiatnium Dioxide (CI 77891). Caprylic/Capric Triglyceride, Phenyl Trimethicone, Methyl Trimethicone, Aluminum Oxide, Lauryl PEG-10 Tris(Trimethylsiloxysiloxy)silyethyl Dimethicone, Trimethylsiloxysilicate, Dimethicone, Butylene Glycol, Glycerin, Gold, Palmitoyl Hexapeptide-14, Peat Extract, Diglucosyl Gallic Acid, Hydroxyethylcellulose, Saccharomyces/Xylinum/Black Tea Ferment, HDI/Trimethylol Hexyllactone Crosspolymer, Polymethylsilsesquioxane, Triethoxycaprylylsilane, Bis-Stearyl Dimethicone, PEG-9 Polydimethylsiloxyethyl Dimethicone, Dimethicone/PEG-10/15 Crosspolymer, Dextrin Palimitate, Caprylyl Methicone, Cetyl PEG/PPG-10/1 Dimethicone, Polyglyceryl-3Beeswax, Silica, Mica (CI 77019), Ethoxydiglycol, Magnesium Sulfate, Caprylyl Glycol, Ethylhexylglycerin, Hexylene Glycol, Phenoxyethanol, Tetrasodium EDTA, Potassium Sorabate, Talc, May Contain

Barium Sulfate (CI 77120), Bismuth Oxychloride (CI 77163), Iron Oxides (CI 77489, CI 77491, CI 77492, CI 77499), Ultramarines (CI 77007)

PACKAGE LABEL

Timeless Illuminating Makeup

Broad Spectrum SPF 30

Merle Norman

30 mL e 1 FL. OZ.